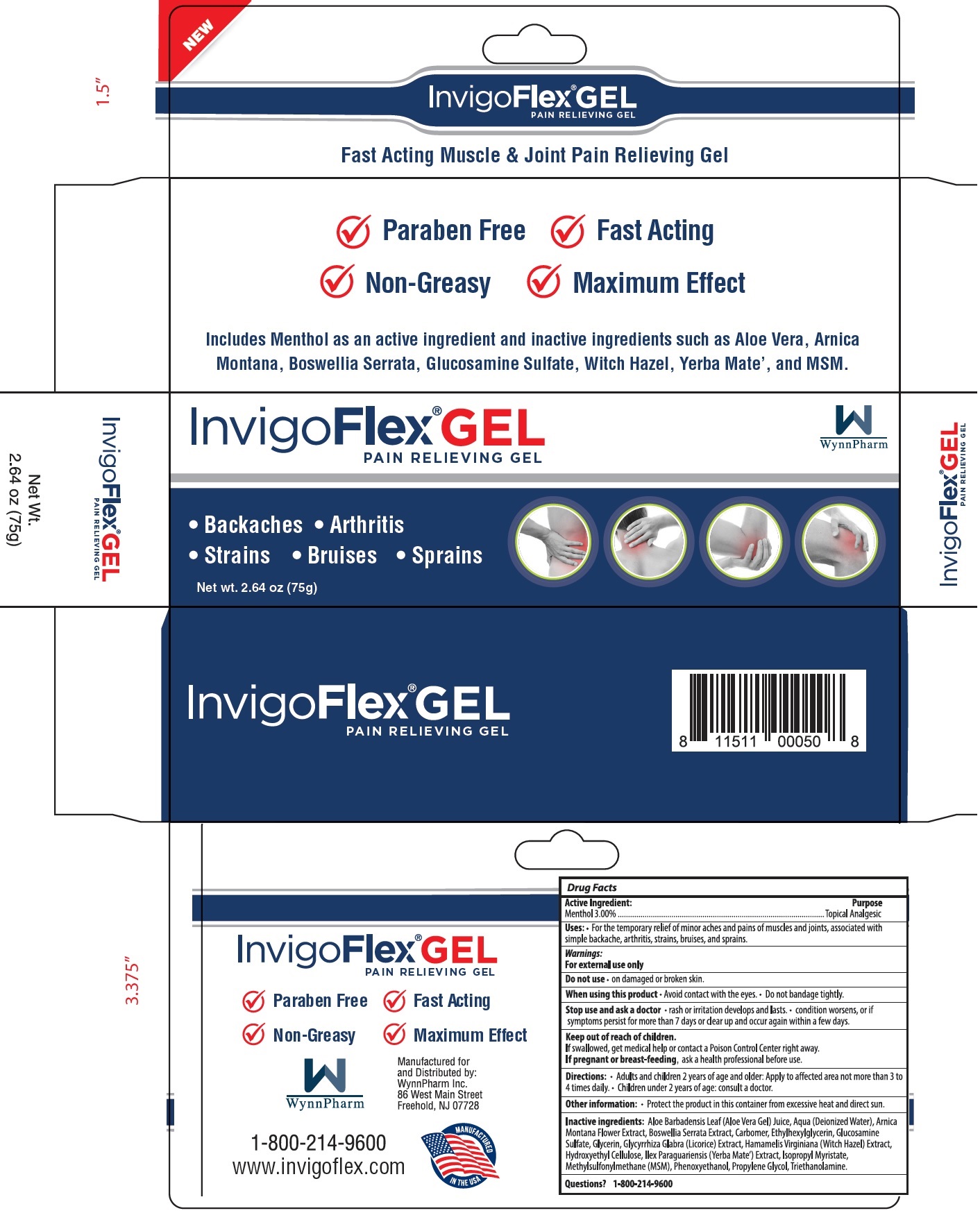 DRUG LABEL: INVIGO FLEX Pain Relief Gel
NDC: 35324-276 | Form: GEL
Manufacturer: WYNNPHARM INC.
Category: otc | Type: HUMAN OTC DRUG LABEL
Date: 20231110

ACTIVE INGREDIENTS: MENTHOL 30 mg/1 g
INACTIVE INGREDIENTS: ALOE VERA LEAF; WATER; ARNICA MONTANA FLOWER; INDIAN FRANKINCENSE; CARBOMER HOMOPOLYMER, UNSPECIFIED TYPE; ETHYLHEXYLGLYCERIN; GLUCOSAMINE SULFATE; GLYCERIN; GLYCYRRHIZA GLABRA; HAMAMELIS VIRGINIANA TOP; HYDROXYETHYL CELLULOSE, UNSPECIFIED; ILEX PARAGUARIENSIS LEAF; ISOPROPYL MYRISTATE; DIMETHYL SULFONE; PHENOXYETHANOL; PROPYLENE GLYCOL; TROLAMINE

INVIGO FLEX GEL Pain Relief Gel

Active Ingredient:

Menthol 3.00%

Purpose

Topical Analgesic

Uses:

For the temporary relief of minor aches and pains of muscles and joints associated with: simple backache, arthritis, strains, bruises, sprains.

Warnings:

For external use only

Do not use

• on damaged or broken skin.

When using this product

• Avoid contact with the eyes. • Do not bandage tightly.

Stop use and ask a doctor

• rash or irritation develops and lasts. • condition worsens, or if symptoms persist for more than 7 days or clears up and occur again within a few days.

Keep out of reach of children.

If swallowed, get medical help or contact a Poison Control Center right away.

If pregnant or breast-feeding,

ask a health professional before use.

Directions

• Adults and children 2 years of age and older: Apply to affected area not more than 3 to 4 times daily.

• Children under 2 years of age: consult a doctor.

Other information

• Protect the product in this container from excessive heat and direct sun.

Inactive Ingredients:

Aloe Barbadensis Leaf (Aloe Vera Gel) Juice, Aqua (Deionized Water), Arnica Montana Flower Extract, Boswellia Serrata Extract, Carbomer, Ethylhexylglycerin, Glucosamine Sulfate, Glycerin, GLycyrrhiza Glabra (Licorice) Extract, Hamamelis Virginiana (Witch Hazel) Extract, Hydroxyethyl Cellulose, Ilex Paraguariensis (Yerba Mate') Extract, Isopropyl Myristate, Methylsulfonulmethane (MSM), Phenoxyethanol, Propylene Glycol, Triethanolamine.

Questions?

1-800-214-9600